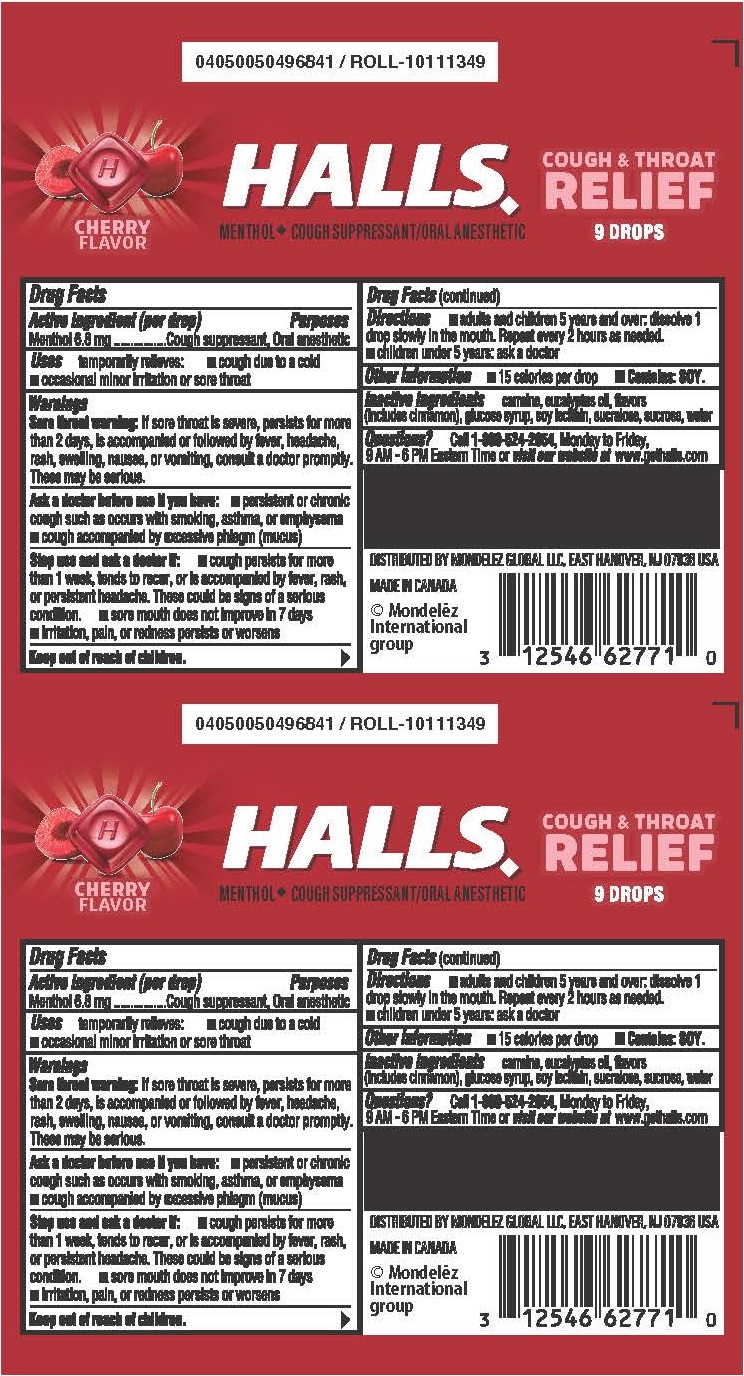 DRUG LABEL: Halls
NDC: 12546-333 | Form: LOZENGE
Manufacturer: Mondelez Global LLC
Category: otc | Type: HUMAN OTC DRUG LABEL
Date: 20250616

ACTIVE INGREDIENTS: MENTHOL 6.8 mg/1 1
INACTIVE INGREDIENTS: EUCALYPTUS OIL; CARMINIC ACID; LECITHIN, SOYBEAN; SUCRALOSE; SUCROSE; WATER; CORN SYRUP

HALLS Cherry stick

Active Ingredient

<(per drop) Menthol 6.8 mg>

Purposes

<Cough suppressant, Oral anesthetic>

Uses

<Temporarily relieves:

- cough due to a cold
- ocassional minor irritation or sore throat>

Warnings

<Sore throat warning: if sore throat is severe, persists for more than 2 days, is accompanied or followed by fever, headache, rash, swelling, nausea, or vomiting, consult a doctor promptly. These may be serious.>

Ask a doctor before use if you have

- persistent or chronic cough such as occurs with smoking, asthma, or emphysema
- cough accompanied by excessive phlegm (mucus)

Stop use and ask a doctor if

- cough persists for more than 1 week, tends to recur, or is accompanied by fever, rash or persistent headache. These could be signs of a serious condition.
- sore mouth does not improve in 7 days
- irritation, pain, or redness persists or worsens

Directions

- adults and children 5 years and over: dissolve 1 drop slowly in the mouth. Repeat every 2 hours as needed.
- children under 5 years: ask a doctor

Other information

- 15 calories per drop
- Contains: SOY.

Inactive ingredients

<carmine, eucalyptus oil, flavors (includes cinnamon), glucose syrup, soy lecithin, sucralose, sucrose, water>

Questions

<Call 1-800-524-2854, Monday to Friday, 9AM-6PM Eastern Time or visit our website at www.gethalls.com>